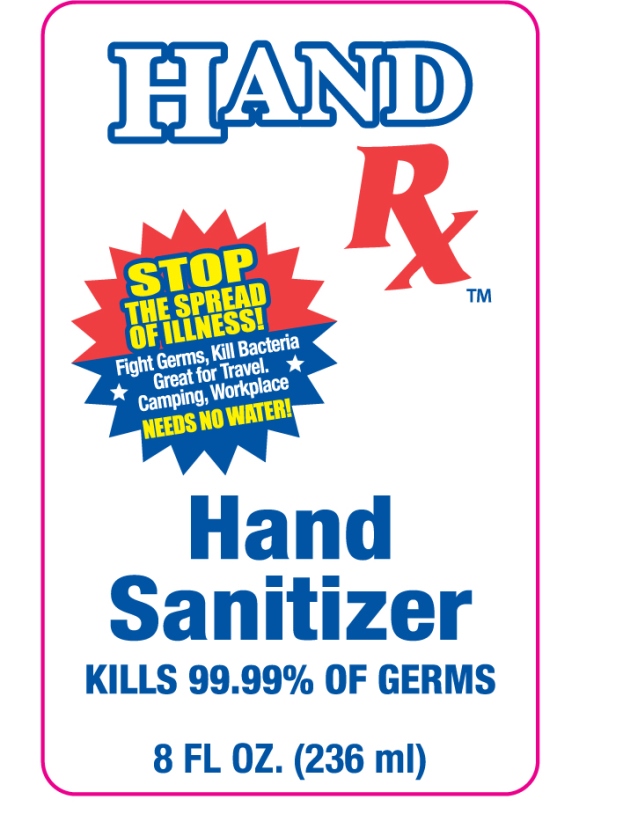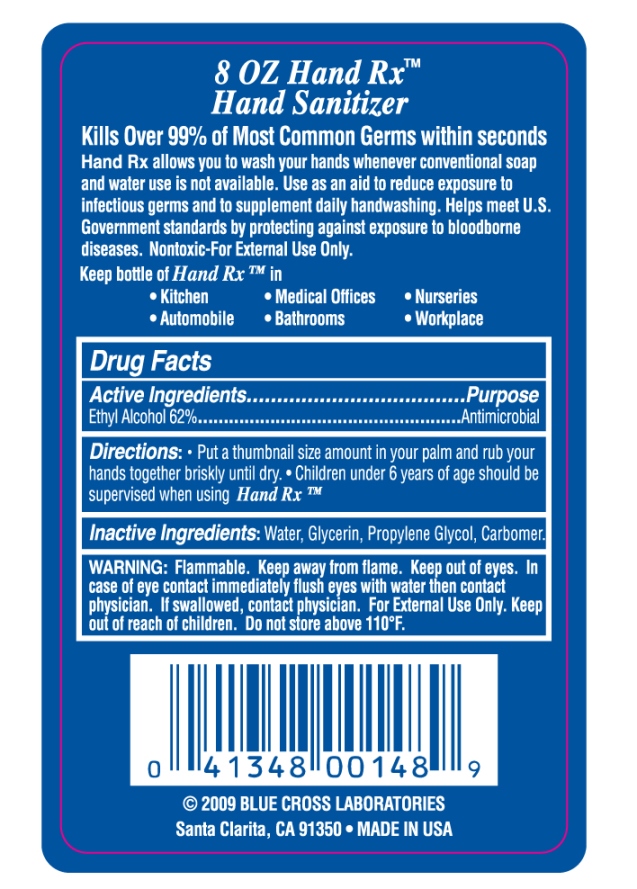 DRUG LABEL: Hand Sanitizer
NDC: 22431-581 | Form: LIQUID
Manufacturer: Blue Cross Laboratories, Inc.
Category: otc | Type: HUMAN OTC DRUG LABEL
Date: 20200710

ACTIVE INGREDIENTS: ALCOHOL 62 g/100 mL
INACTIVE INGREDIENTS: WATER; GLYCERIN; PROPYLENE GLYCOL; CARBOMER HOMOPOLYMER, UNSPECIFIED TYPE

Hand Rx Hand Sanitizer

Active ingredients purpose

Ethyl Alcohol 62% Antimicrobial

PURPOSE

Kills over 99% of most common germs

Keep out of reach of children

INDICATIONS AND USAGE

Keep out of eyes.In case of eye contact immediately flush eyes with water then contact physician.

WARNINGS

Warning: flammable. Keep away from flame. If swallowed, contact physician. For external use only. Do not store above 110 degrees farenheit.

directions:

put a thumbnail size amount in your palm and rub your hands together briskly until dry

Children under 6 years of age should be supervised when using Hand Rx.

Inactive Ingredients: Water, Glycerin, Propylene Glycol, Carbomer

PACKAGE LABEL

Hand Rx

Hand Sanitizer

Kills 99.99% of germs

8 Fl Oz. (236 ml)